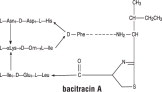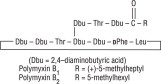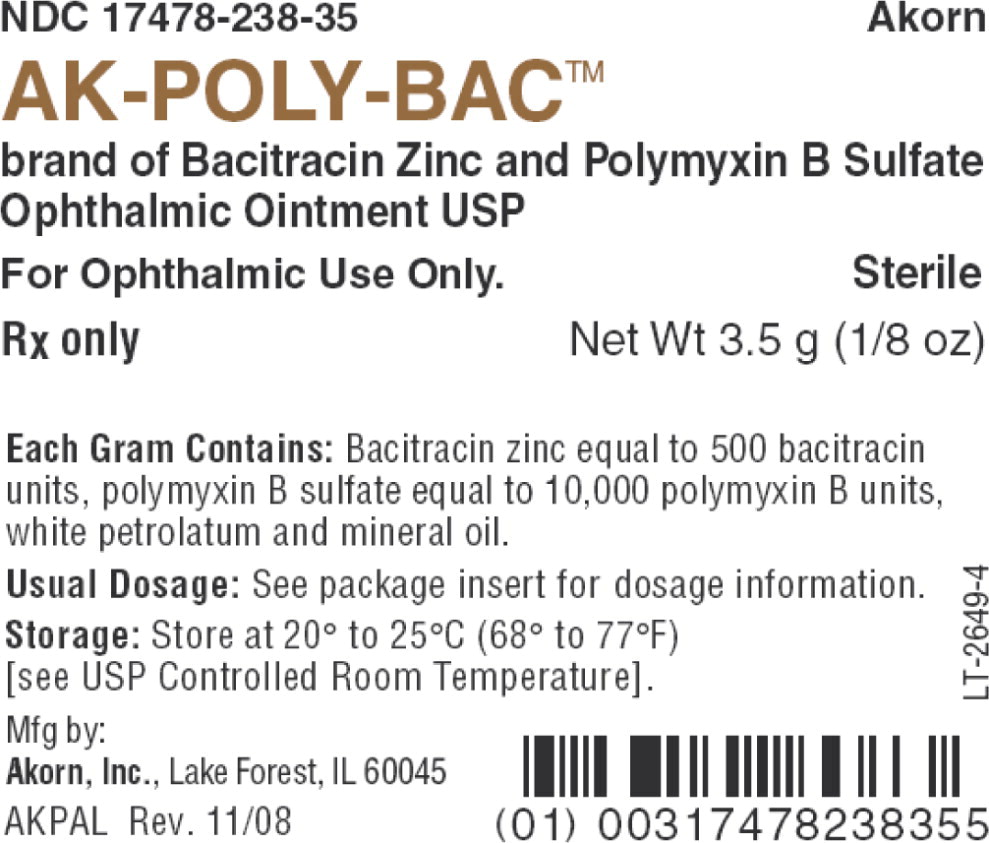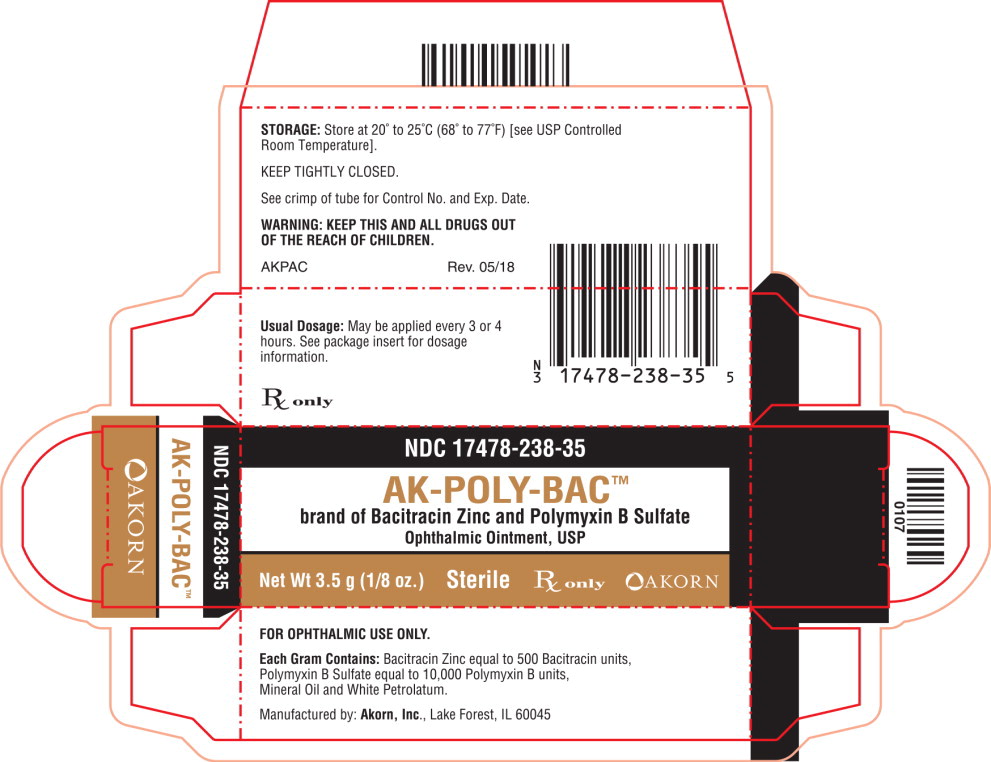 DRUG LABEL: AK-POLY-BAC
NDC: 17478-238 | Form: OINTMENT
Manufacturer: Akorn
Category: prescription | Type: HUMAN PRESCRIPTION DRUG LABEL
Date: 20201008

ACTIVE INGREDIENTS: Bacitracin Zinc 500 [USP'U]/1 g; Polymyxin B Sulfate 10000 [USP'U]/1 g
INACTIVE INGREDIENTS: Mineral Oil; Petrolatum

Bacitracin Zinc and Polymyxin B Sulfate Ophthalmic Ointment USP, Sterile

Rx only

DESCRIPTION:

Bacitracin Zinc and Polymyxin B Sulfate Ophthalmic Ointment is a sterile antimicrobial ointment for ophthalmic use.

Bacitracin zinc is the zinc salt of bacitracin, a mixture of related cyclic polypeptides (mainly bacitracin A) produced by the growth of an organism of the licheniformis group of Bacillus subtilis var Tracy. It has a potency of not less than 40 bacitracin units per mg. The structural formula for bacitracin A is:

Polymyxin B Sulfate is the sulfate salt of polymyxin B1 and B2 which are produced by the growth of Bacillus polymyxa (Prazmowski) Migula (Fam. Bacillaceae). It has a potency of not less than 6,000 polymyxin B units per mg, calculated on an anhydrous basis. The structural formulae are:

Each gram contains: Bacitracin zinc equal to 500 bacitracin units and polymyxin B sulfate equal to 10,000 polymyxin B units, white petrolatum and mineral oil.

CLINICAL PHARMACOLOGY:

Polymyxin B attacks gram-negative bacilli, including virtually all strains of Pseudomonas aeruginosa and H influenzae species.

Bacitracin is active against most gram-positive bacilli and cocci including hemolytic streptococci.

INDICATIONS AND USAGE:

For the treatment of superficial ocular infections involving the conjunctiva and/or cornea caused by organisms susceptible to bacitracin zinc and polymyxin B sulfate.

CONTRAINDICATIONS:

This product is contraindicated in those individuals who have shown hypersensitivity to any of its components.

WARNINGS:

Ophthalmic ointments may retard corneal healing.

PRECAUTIONS:

As with other antibiotic preparations, prolonged use may result in overgrowth of nonsusceptible organisms, including fungi. Appropriate measures should be taken if this occurs.

DOSAGE AND ADMINISTRATION:

Apply the ointment every 3 or 4 hours for 7 to 10 days, depending on the severity of the infection.

HOW SUPPLIED:

Bacitracin Zinc and Polymyxin B Sulfate ophthalmic ointment USP, sterile, each gram contains bacitracin zinc equal to 500 bacitracin units and polymyxin B sulfate equal to 10,000 polymyxin B units, in a tube of 3.5 g (1/8 oz) with ophthalmic tip.

NDC 17478-238-35

STORAGE:

Store at 20° to 25°C (68° to 77°F) [see USP Controlled Room Temperature].

Akorn
Manufactured By: Akorn, Inc.
Lake Forest, IL 60045
AKP00N
Rev. 06/16

Principal Display Panel Text for Container Label:

NDC 17478-238-35 Akorn

AK-POLY-BAC™

brand of Bacitracin Zinc and Polymyxin B Sulfate

Ophthalmic Ointment USP

For Ophthalmic Use Only. Sterile

Rx only Net Wt 3.5 g (1/8 oz)

Principal Display Panel Text for Carton Label:

NDC 17478-238-35

AK-POLY-BAC™

brand of Bacitracin Zinc and Polymyxin B Sulfate

Ophthalmic Ointment, USP

Net Wt 3.5 g (1/8 oz.) Sterile Rx only Akorn Logo